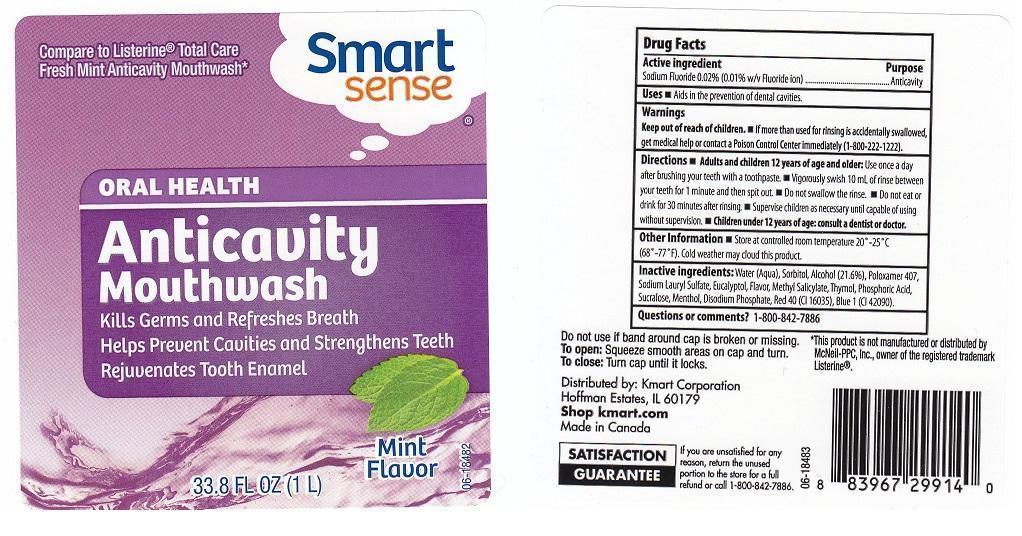 DRUG LABEL: SMART SENSE
NDC: 49738-552 | Form: LIQUID
Manufacturer: KMART CORPORATION
Category: otc | Type: HUMAN OTC DRUG LABEL
Date: 20130509

ACTIVE INGREDIENTS: SODIUM FLUORIDE 0.2 mg/1 mL
INACTIVE INGREDIENTS: WATER; SORBITOL; ALCOHOL; POLOXAMER 407; SODIUM LAURYL SULFATE; EUCALYPTOL; METHYL SALICYLATE; THYMOL; PHOSPHORIC ACID; SUCRALOSE; MENTHOL; SODIUM PHOSPHATE, DIBASIC, ANHYDROUS; FD&C RED NO. 40; FD&C BLUE NO. 1

DRUG FACTS

ACTIVE INGREDIENT

SODIUM FLUORIDE 0.02% (0.01% W/V FLUORIDE ION)

PURPOSE

ANTICAVITY

USES

AIDS IN THE PREVENTION OF DENTAL CAVITIES.

WARNINGS

KEEP OUT OF REACH OF CHILDREN. IF MORE THAN USED FOR RINSING IS ACCIDENTALLY SWALLOWED, GET MEDICAL HELP OR CONTACT A POISON CONTROL CENTER IMMEDIATELY (1-800-222-1222).

KEEP OUT OF REACH OF CHILDREN

IF MORE THAN USED FOR RINSING IS ACCIDENTALLY SWALLOWED, GET MEDICAL HELP OR CONTACT A POISON CONTROL CENTER IMMEDIATELY (1-800-222-1222).

DIRECTIONS

ADULTS AND CHILDREN 12 YEARS OF AGE AND OLDER: USE ONCE A DAY AFTER BRUSHING YOUR TEETH WITH A TOOTHPASTE. VIGOROUSLY SWISH 10 ML OF RINSE BETWEEN YOUR TEETH FOR 1 MINUTE AND THEN SPIT OUT. DO NOT SWALLOW THE RINSE. DO NOT EAT OR DRINK FOR 30 MINUTES AFTER RINSING. SUPERVISE CHILDREN AS NECESSARY UNTIL CAPABLE OF USING WITHOUT SUPERVISION. CHILDREN UNDER 12 YEARS OF AGE: CONSULT A DENTIST OR DOCTOR.

OTHER INFORMATION

STORE AT CONTROLLED ROOM TEMPERATURE 20-25C (68-77F). COLD WEATHER MAY CLOUD THIS PRODUCT.

INACTIVE INGREDIENTS:

WATER (AQUA), SORBITOL, ALCOHOL (21.6%), POLOXAMER 407, SODIUM LAURYL SULFATE, EUCALYPTOL, FLAVOR, METHYL SALICYLATE, THYMOL, PHOSPHORIC ACID, SUCRALOSE, MENTHOL, DISODIUM PHOSPHATE, RED 40 (CI 16035), BLUE 1 (CI 42090).

QUESTIONS OR COMMENTS?

1-800-842-7886